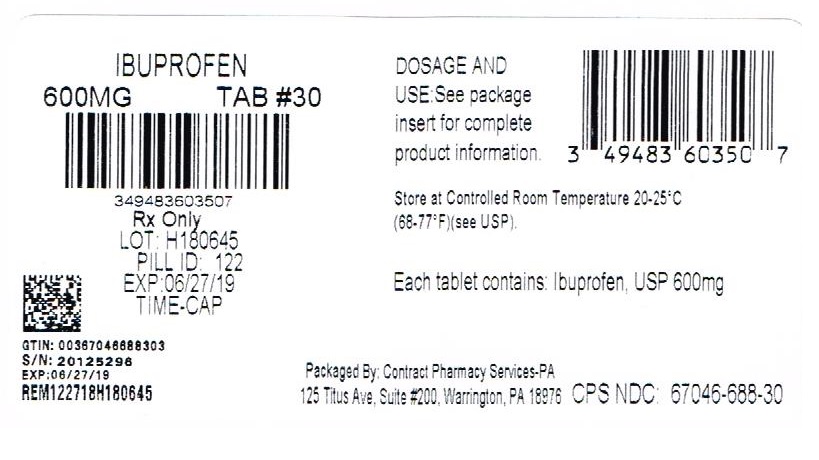 DRUG LABEL: Ibuprofen
NDC: 67046-688 | Form: TABLET, FILM COATED
Manufacturer: Contract Pharmacy Services-PA
Category: prescription | Type: HUMAN PRESCRIPTION DRUG LABEL
Date: 20181229

ACTIVE INGREDIENTS: IBUPROFEN 600 mg/1 1

Ibuprofen 600mg USP 688

PATIENT INFORMATION

TIME CAP LABORATORIES, INC TIME CAP LABORATORIES, INC MARKSANS PHARMA LIMITED IBUPROFEN IBUPROFEN IBUPROFEN IBUPROFEN COLLOIDAL SILICON DIOXIDE CROSCARMELLOSE SODIUM MAGNESIUM STEARATE CELLULOSE, MICROCRYSTALLINE POLYETHYLENE GLYCOLS POLYVINYL ALCOHOL STARCH, PREGELATINIZED CORN TALC TITANIUM DIOXIDE 121 IBUPROFEN IBUPROFEN IBUPROFEN IBUPROFEN COLLOIDAL SILICON DIOXIDE CROSCARMELLOSE SODIUM MAGNESIUM STEARATE CELLULOSE, MICROCRYSTALLINE POLYETHYLENE GLYCOLS POLYVINYL ALCOHOL STARCH, PREGELATINIZED CORN TALC TITANIUM DIOXIDE 122 IBUPROFEN IBUPROFEN IBUPROFEN IBUPROFEN COLLOIDAL SILICON DIOXIDE CROSCARMELLOSE SODIUM MAGNESIUM STEARATE CELLULOSE, MICROCRYSTALLINE POLYETHYLENE GLYCOLS POLYVINYL ALCOHOL STARCH, PREGELATINIZED CORN TALC TITANIUM DIOXIDE 123 HOW SUPPLIED 400mg (white to of white, round, biconvex, film coated tablets debossed with '121' on one side and plain on the other side) Bottles of 100 & 500 HOW SUPPLIED 600mg (white to off white, capsule shaped, biconvex, film coated tablets debossed with '122' on one side and plain on the other side) Bottles of 30, 50, 100 & 500 800mg (white to off white, capsule shaped, biconvex, film coated tablets debossed with '123' on one side and plain on the other side) Bottles of 30, 50, 100 & 500 400mg Ibuprofen Package Label image description 600mg Ibuprofen Package Label image description 800mg Ibuprofen Package Label image description REPACKAGED BY: COUPLER ENTERPRISES INC. NDJA 4/19/18